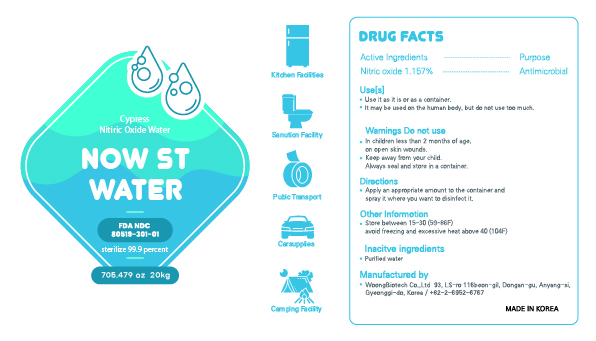 DRUG LABEL: NOW st
NDC: 80519-301 | Form: LIQUID
Manufacturer: Korea Electrotechnology Green Labs
Category: otc | Type: HUMAN OTC DRUG LABEL
Date: 20221116

ACTIVE INGREDIENTS: NITRIC OXIDE 1.1157 g/100 mL
INACTIVE INGREDIENTS: WATER 98.843 mL/100 mL

Active Ingredients

Nitric oxide

USE

Use it as it is or as a container.

It is harmless to use on the human body, but do not use it as much as possible.

directions

Apply an appropriate amount to the container and spray it where you want to disinfect it.

Keep out of reach of children

Warnings

do not use

- in children less than 2 months of age.
- on open skin wounds.
- Keep away from your child.
- Always seal and store in a container.

Other information

- store between 15~30 (59~86F)
- avoid freezing and excessive heat above 40 (104F)

question

WoongBiotech Co.,Ltd 93, LS-ro 116beon-gil, Dongan-gu,
Anyang-si, Gyeonggi-do, Korea
+82-2-6952-6767

Stop use and ask doctor

If you have swallowed it or have an allergic reaction to your skin, stop using it and consult a doctor.

Inactive ingredient

purified water

PURPOSE

Antimicrobial

label

80519-301-01